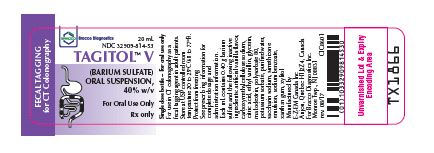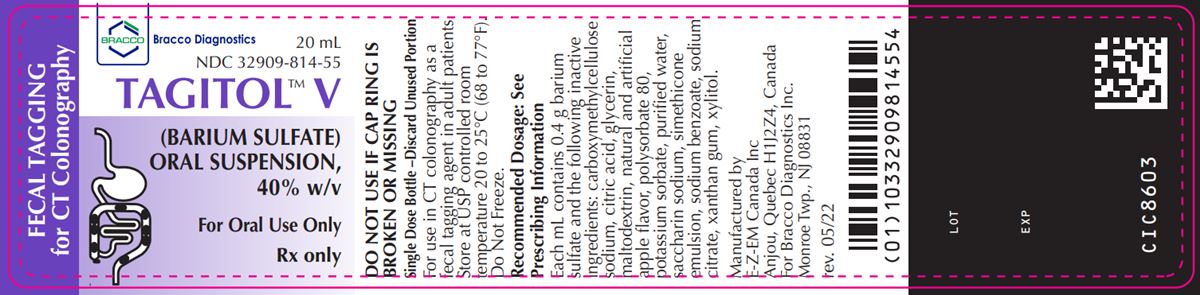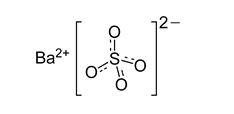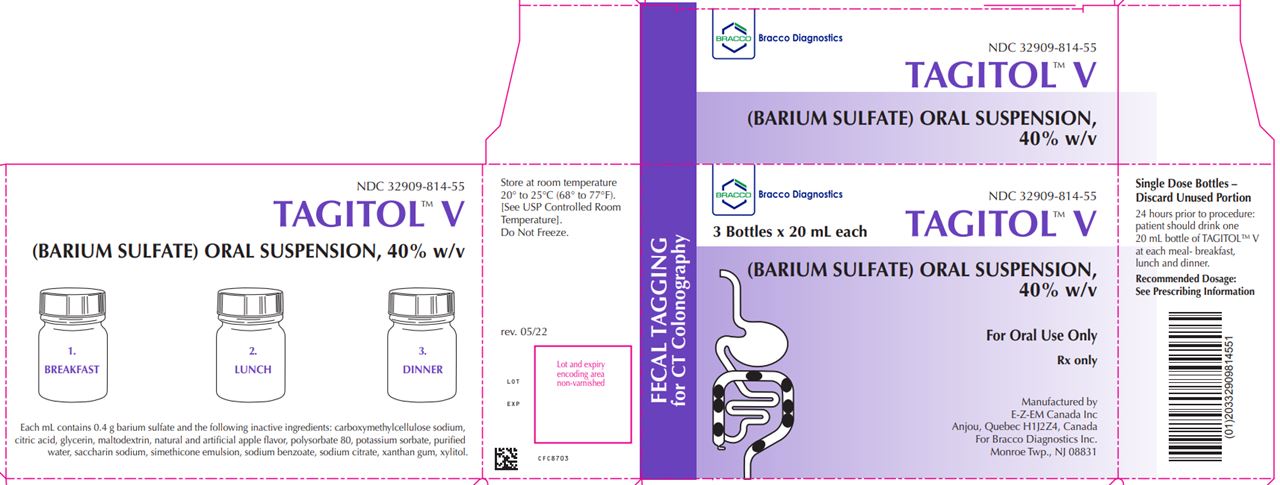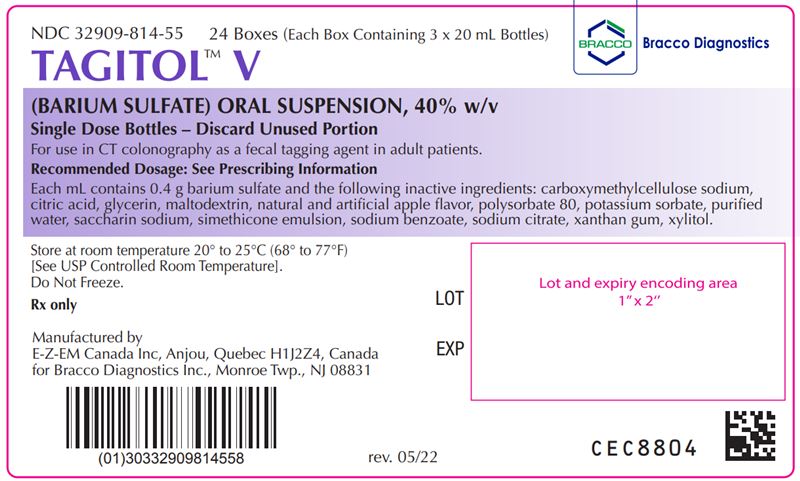 DRUG LABEL: Tagitol V
NDC: 32909-814 | Form: SUSPENSION
Manufacturer: E-Z-EM Canada Inc
Category: prescription | Type: HUMAN PRESCRIPTION DRUG LABEL
Date: 20221026

ACTIVE INGREDIENTS: Barium Sulfate 400 mg/1 mL
INACTIVE INGREDIENTS: anhydrous citric acid; dimethicone 350; dimethicone 1000; glycerin; maltodextrin; polysorbate 80; potassium sorbate; saccharin sodium; silicon dioxide; sodium benzoate; trisodium citrate dihydrate; water; xanthan gum; xylitol; CARBOXYMETHYLCELLULOSE SODIUM, UNSPECIFIED FORM

HIGHLIGHTS OF PRESCRIBING INFORMATION

These highlights do not include all the information needed to use TAGITOL V safely and effectively. See full prescribing information for TAGITOL V.
TAGITOL V (barium sulfate) oral suspension
Initial U.S. Approval: 2016

1 INDICATIONS AND USAGE

TAGITOL V is a radiographic contrast agent indicated in adult patients for use in computed tomography (CT) colonography as a fecal tagging agent (1)

2 DOSAGE AND ADMINISTRATION

- The recommended dose is:
  - One 20 mL bottle (8g barium sulfate) with each meal (breakfast, lunch and dinner) the day before the CT colonography examination (2.1).
  - Total dose = 3 bottles (24 g barium sulfate)
- For oral use only (2.2).

3 DOSAGE FORMS AND STRENGTHS

- Oral suspension : barium sulfate (40% w/v) 20 mL single dose bottles as a ready to use suspension for oral administration (3)

4 CONTRAINDICATIONS

TAGITOL V is contraindicated in patients with:

- Known or suspected perforation of the gastrointestinal (GI) tract (4)
- Known obstruction of the GI tract (4)
- Conditions associated with high risk of GI perforation or aspiration (4)
- Known hypersensitivity to barium sulfate or any of the excipients of TAGITOL V (4)

5 WARNINGS AND PRECAUTIONS

- Hypersensitivity reactions: Emergency equipment and trained personnel should be immediately available (5.1)
- Intra-abdominal barium leakage: May occur in conditions which increase the risk of perforation such as - carcinoma, GI fistula, inflammatory bowel disease, gastric or duodenal ulcer, appendicitis, diverticulitis, or severe stenosis or obstructing lesions of the GI tract (5.2)
- Delayed GI transit and obstruction: Patients should maintain adequate hydration in days following a barium sulfate procedure to avoid obstruction or impaction by baroliths (5.3)
- Aspiration pneumonitis: Caution is recommended in patients with a history of food aspiration and in patients with known swallowing disorders (5.4)

6 ADVERSE REACTIONS

Common adverse reactions include nausea, vomiting, diarrhea and abdominal cramping (6)

To report SUSPECTED ADVERSE REACTIONS, contact Bracco Diagnostics Inc at 1-800-257-5181 or FDA at 1-800-FDA-1088 or www.fda.gov/medwatch

FULL PRESCRIBING INFORMATION

1 INDICATIONS AND USAGE

TAGITOL V is indicated for use in adult patients for use in computed tomography (CT) colonography as a fecal tagging agent.

2 DOSAGE AND ADMINISTRATION

2.1 Recommended Dosing

- The recommended oral dose of TAGITOL V is one 20 mL bottle (8 g barium sulfate) with each meal (breakfast, lunch and dinner) the day before the colonography examination. Total dose = 3 bottles (24 g barium sulfate).

2.2 Important Administration Instructions

- TAGITOL V is typically provided to the patient for self-administration. Advise patients to carefully read and follow the Patient Instructions for Use to be provided to the patient.
- Shake bottle for 15 seconds prior to administration.
- For oral use only.
- Encourage patients to hydrate following the barium sulfate procedure.
- Discard any unused suspension.

3 DOSAGE FORMS AND STRENGTHS

Oral suspension: barium sulfate (40% w/v) supplied as a ready-to-use suspension in a 20 mL, single-dose, bottle for oral administration. Each 20 mL bottle contains 8 g of barium sulfate.

4 CONTRAINDICATIONS

TAGITOL V is contraindicated in patients with:

-   known or suspected perforation of the gastrointestinal (GI) tract;

-   known obstruction of the GI tract;

-   high risk of GI perforation such as those with a recent GI perforation, acute GI hemorrhage or ischemia, toxic megacolon, severe ileus, post GI surgery or biopsy, acute GI injury or burn, or recent radiotherapy to the pelvis;

-   high risk of aspiration such as those with prior aspiration, tracheo-esophageal fistula, or obtundation;

-   known hypersensitivity to barium sulfate or any of the excipients of TAGITOL V.

5 WARNINGS AND PRECAUTIONS

5.1 Hypersensitivity Reactions

Barium sulfate preparations contain a number of excipients, including natural and artificial flavors and may induce serious hypersensitivity reactions. The manifestations include hypotension, bronchospasm and other respiratory impairments, dermal reactions including rashes, urticaria and itching. A history of bronchial asthma, atopy, or a previous reaction to a contrast agent may increase the risk for hypersensitivity reactions. Emergency equipment and trained personnel should be immediately available for treatment of a hypersensitivity reaction.

5.2 Intra-abdominal Barium Leakage

The use of TAGITOL V is contraindicated in patients at high risk of perforation of the GI tract [see Contraindications (4)]. Administration of TAGITOL V may result in leakage of barium from the GI tract in the presence of conditions that increase the risk of perforation such as carcinomas, GI fistula, inflammatory bowel disease, gastric or duodenal ulcer, appendicitis, or diverticulitis, and in patients with a severe stenosis at any level of the gastrointestinal tract, especially if it is distal to the stomach. The barium leakage has been associated with peritonitis and granuloma formation.

5.3 Delayed Gastrointestinal Transit and Obstruction

Orally administered barium sulfate may accumulate proximal to a constricting lesion of the colon, causing obstruction or impaction with development of baroliths (inspissated barium associated with feces) and may lead to abdominal pain, appendicitis, bowel obstruction, or rarely perforation. Patients with the following conditions are at higher risk for developing obstruction or baroliths: severe stenosis at any level of the GI tract, impaired gastrointestinal motility, electrolyte imbalance, dehydration, on a low residue diet, on medications that delay GI motility, constipation, cystic fibrosis, Hirschsprung disease, and the elderly. To reduce the risk of delayed GI transit and obstruction, patients should maintain adequate hydration following a barium sulfate procedure.

5.4 Aspiration Pneumonitis

The use of TAGITOL V is contraindicated in patients at high risk of aspiration [see Contraindications (4)]. Oral administration of barium is associated with aspiration pneumonitis, especially in patients with a history of food aspiration or with compromised swallowing mechanism. Vomiting following oral administration of barium sulfate may lead to aspiration pneumonitis.

5.5 Systemic Embolization

Barium sulfate products may occasionally intravasate into the venous drainage of the large bowel and enter the circulation as a "barium embolus" leading to potentially fatal complications which include systemic and pulmonary embolism, disseminated intravascular coagulation, septicemia and prolonged severe hypotension. Although this complication is exceedingly uncommon after oral administration of barium sulfate products, monitor patients for potential intravasation when administering barium sulfate.

6 ADVERSE REACTIONS

The following adverse reactions have been identified from spontaneous reporting or clinical studies of barium sulfate administered orally. Because the reactions are reported voluntarily from a population of uncertain size, it is not always possible to reliably estimate their frequency or to establish a causal relationship to drug exposure:

- Nausea, vomiting, diarrhea and abdominal cramping
- Serious adverse reactions and fatalities include aspiration pneumonitis, barium sulfate impaction, intestinal perforation with consequent peritonitis and granuloma formation, vasovagal and syncopal episodes.

8 USE IN SPECIFIC POPULATIONS

8.1 Pregnancy

Risk Summary

TAGITOLVis not absorbed systemically following oral administration, and maternal use is not expected to result in fetal exposure to the drug [see Clinical Pharmacology (12.3)].

8.2 Lactation

Risk Summary

TAGITOL V is not absorbed systemically by the mother following oral administration and breastfeeding is not expected to result in exposure of the infant to the drug [see Clinical Pharmacology (12.3)]

8.4 Pediatric Use

TAGITOL V is not indicated for pediatric use.

8.5 Geriatric Use

Clinical studies of TAGITOL V do not include sufficient numbers of subjects aged 65 and over to determine whether they respond differently from younger subjects. Other reported clinical experience has not identified differences in responses between the elderly and younger patients. In general, dose selection for an elderly patient should be cautious, usually starting at the low end of the dosing range, reflecting the greater frequency of decreased hepatic, renal, or cardiac function, and of concomitant disease or other drug therapy.

11 DESCRIPTION

TAGITOL V (barium sulfate) is a radiographic contrast agent that is supplied as a 40% w/v, off-white to lightly colored, free-flowing, ready-to-use suspension with an apple aroma for oral administration. The active ingredient barium sulfate is designated chemically as BaSO4 with a molecular weight of 233.4 g/mol and the following chemical structure:

TAGITOL V contains the following excipients: carboxymethylcellulose sodium, citric acid, glycerin, maltodextrin, natural and artificial apple flavor, polysorbate 80, potassium sorbate, purified water, saccharin sodium, simethicone emulsion, sodium benzoate, sodium citrate, xanthan gum, and xylitol.

12 CLINICAL PHARMACOLOGY

12.1 Mechanism of Action

Due to its high atomic number, barium (the active ingredient in TAGITOL V) is opaque to x-rays and therefore acts as a positive contrast agent for radiographic studies.

12.2 Pharmacodynamics

Barium sulfate is biologically inert and has no known pharmacological effects.

12.3 Pharmacokinetics

Under physiological conditions, barium sulfate passes through the gastrointestinal tract in an unchanged form and is absorbed only in pharmacologically insignificant amounts.

13 NONCLINICAL TOXICOLOGY

13.1 Carcinogenesis, Mutagenesis, Impairment of Fertility

No animal studies have been performed to evaluate the carcinogenic potential of barium sulfate or potential effects on fertility.

16 HOW SUPPLIED/STORAGE AND HANDLING

16.1 How Supplied

TAGITOL V (barium sulfate) is an oral suspension (40% w/v) supplied as a box of three 20 mL bottles. Each bottle contains 8 grams barium sulfate.

Provided as: 24 boxes, each containing 3 (20 mL) bottles (NDC 32909-814)

16.2 Storage and Handling

Store at room temperature 20° to 25°C (68° to 77°F) [See USP Controlled Room Temperature]. Do Not Freeze.

17 PATIENT COUNSELING INFORMATION

After administration, advise patients to:

- Maintain adequate hydration [see Dosage and Administration (2.2) and Warnings and Precautions (5.3)].
- Seek medical attention for worsening of constipation or slow gastrointestinal passage [see Warnings and Precautions (5.3)].
- Seek medical attention for any delayed onset of hypersensitivity: rash, urticaria, or respiratory difficulty [see Warnings and Precautions (5.1)].

Administration Instructions

TAGITOL V is typically provided to the patient for self-administration. Advise patients to carefully read and follow the Patient Instructions for Use to be provided to the patient.

Provide the patient with any site specific instructions regarding their procedure and when to take meals.

Rx only

Manufactured by
EZEM Canada Inc
Anjou (Quebec) Canada H1J 2Z4
For
Bracco Diagnostics Inc.
Monroe Township, NJ 08831

CLC8503
rev. 05/22

INSTRUCTIONS FOR USE

TAGITOL V (tag-i-täl vē)

(barium sulfate)

oral suspension

Read this Instructions for Use before you drink TAGITOL V (barium sulfate) oral suspension. This information does not take the place of talking to your healthcare provider about your medical condition or your treatment.

Important:

Take TAGITOL V exactly as your healthcare provider tells you. Your healthcare provider will prescribe the dose that is right for you. You can ask your healthcare provider or pharmacist if you have any questions about how to take TAGITOL V.

How should I store TAGITOL V?

- Before using TAGITOL V store at room temperature between 68°F and 77°F (20°C and 25°C).
- Do not freeze.

Keep TAGITOL V and all medicines out of the reach of children.

Supplies you will need:

- 1 box containing 3 bottles of TAGITOL V. Each bottle contains 20 mL of TAGITOL V

How should I take TAGITOL V

The day before your procedure you will drink 1 bottle of TAGITOL V with each meal:

- Breakfast: Shake 1 bottle of TAGITOL V for 15 seconds, open the bottle, and drink the liquid with breakfast.
- Lunch: Shake 1 bottle of TAGITOL V for 15 seconds, open the bottle, and drink the liquid with lunch.
- Dinner: Shake 1 bottle of TAGITOL V for 15 seconds, open the bottle, and drink the liquid with dinner.

Throw away any unused TAGITOL V with normal household trash. Do not throw away by flushing down the drain.

What should I do if the TAGITOL V spills?

If you spill the liquid while shaking or drinking it, you can clean it up. TAGITOL V is not harmful and can be thrown away with normal household trash.

If you spilled any of the liquid, check with your healthcare provider to find out if you need to change the date of the appointment for your procedure.

This Instructions for Use has been approved by the U.S. Food and Drug Administration

Approved: August 2017

COE5502

Tagitol V Internal Label
NDC: 32909-814-53

Tagitol V Internal Label
NDC: 32909-814-55

Tagitol V External Label

PACKAGE LABEL

Tagitol V Carton